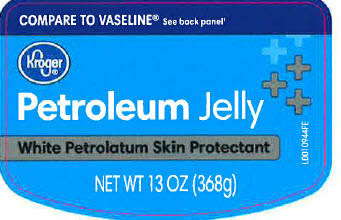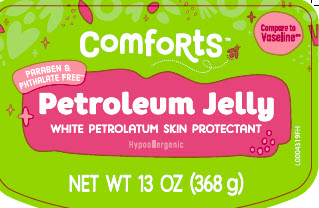 DRUG LABEL: Petroleum
NDC: 30142-069 | Form: JELLY
Manufacturer: The Kroger Co.
Category: otc | Type: HUMAN OTC DRUG LABEL
Date: 20260227

ACTIVE INGREDIENTS: PETROLATUM 1 g/1 g

Kroger_Comforts 069.001/069AA
Petroleum Jelly

Active ingredients

White petrolatum USP (100%)

Purpose

Skin Protectant

Uses

- temporarily protects minor: cuts - scrapes - burns
- temporarily protects and helps relieve chapped or cracked skin and lips
- helps protect from the drying effects of wind and cold weather

Warnings

For external use only

When using this product

- do not get into eyes

See a doctor if

condition lasts more than 7 days.

do not use on

- deep or puncture wounds
- animal bites
- serious burns

Keep out of reach of children.

If swallowed, get medical help or contact a Poison Control Center right away.

Directions

apply as needed

Inactive ingredients

none

Adverse Reactions

DIST. BY THE KROGER CO.

CINCINNATI, OHIO 45202

QUALITY GUARANTEE

800-632-6900

www.kroger.com

PLEASE RECYCLE

Disclaimer

Vaseline® is a registred trademark of Unilever, Greenwich, CT 06830. Unilever is not affiliated with The Kroger Co. or this product.

Principal display panel

COMPARE TO VASELINE® See back panel*

Kroger®

Petroleum Jelly

White Petrolatum Skin Protectant

NET WT 13 OZ (368g)

Principal display panel

Compare to Vaseline®*

Comforts

PARABEN & PHTHALATE FREE**

Petroleum Jelly

WHITE PETROLATUM SKIN PROTECTANT

Hypoallergenic

NET WT 13 OZ (368 g)